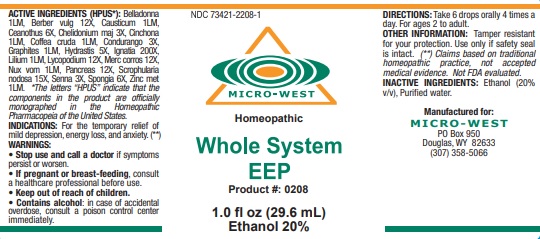 DRUG LABEL: Whole System Eep
NDC: 73421-2208 | Form: LIQUID
Manufacturer: White Manufacturing Inc. DBA Micro-West
Category: homeopathic | Type: HUMAN OTC DRUG LABEL
Date: 20221202

ACTIVE INGREDIENTS: ATROPA BELLADONNA 1 [hp_M]/29.6 mL; BERBERIS VULGARIS ROOT BARK 12 [hp_X]/29.6 mL; CAUSTICUM 1 [hp_M]/29.6 mL; CEANOTHUS AMERICANUS LEAF 6 [hp_X]/29.6 mL; CHELIDONIUM MAJUS WHOLE 3 [hp_X]/29.6 mL; CINCHONA BARK 1 [hp_M]/29.6 mL; ARABICA COFFEE BEAN 1 [hp_M]/29.6 mL; MARSDENIA CONDURANGO BARK 3 [hp_X]/29.6 mL; GRAPHITE 1 [hp_M]/29.6 mL; GOLDENSEAL 5 [hp_X]/29.6 mL; STRYCHNOS IGNATII SEED 200 [hp_X]/29.6 mL; LILIUM LANCIFOLIUM WHOLE FLOWERING 1 [hp_M]/29.6 mL; LYCOPODIUM CLAVATUM SPORE 12 [hp_X]/29.6 mL; MERCURIC CHLORIDE 12 [hp_X]/29.6 mL; STRYCHNOS NUX-VOMICA SEED 1 [hp_M]/29.6 mL; SUS SCROFA PANCREAS 12 [hp_X]/29.6 mL; SCROPHULARIA NODOSA WHOLE 15 [hp_X]/29.6 mL; SENNA LEAF 3 [hp_X]/29.6 mL; SPONGIA OFFICINALIS SKELETON, ROASTED 6 [hp_X]/29.6 mL; ZINC 1 [hp_M]/29.6 mL
INACTIVE INGREDIENTS: ALCOHOL; WATER

Whole System EEP

ACTIVE INGREDIENT

ACTIVE INGREDIENTS (HPUS*): Belladonna 1LM, Berber vulg 12X, Causticum 1LM, Ceanothus 6X, Chelidonium maj 3X, Cinchona
1LM, Coffea cruda 1LM, Condurango 3X, Graphites 1LM, Hydrastis 5X, Ignatia 200X, Lilium 1LM, Lycopodium 12X, Merc corros 12X,
Nux vom 1LM, Pancreas 12X, Scrophularia nodosa 15X, Senna 3X, Spongia 6X, Zinc met 1LM.

*The letters “HPUS” indicate that the components in the product are officially monographed in the Homeopathic Pharmacopeia of the United States.

(**) Claims based on traditional homeopathic practice, not accepted medical evidence. Not FDA evaluated.

INDICATIONS AND USAGE

INDICATIONS: For the temporary relief of mild depression, energy loss, and anxiety. (**)

WARNINGS:
• Stop use and call a doctor if symptoms persist or worsen.
• I f pregnant or breast-feeding, consult a healthcare professional before use.
• Keep out of reach of children.
• Contains alcohol: in case of accidental overdose, consult a poison control center
immediately.

• Keep out of reach of children.

DOSAGE AND ADMINISTRATION

DIRECTIONS: Take 6 drops orally 4 times a day. For ages 2 to adult.

OTHER INFORMATION: Tamper resistant for your protection. Use only if safety seal is intact.

INACTIVE INGREDIENTS: Ethanol (20% v/v), Purified water.

QUESTIONS

Manufactured for:
MICRO-WEST
PO Box 950
Douglas, WY 82633
(307) 358-5066

PACKAGE LABEL

NDC 73421-2208-1

MICRO-WEST

Homeopathic

Whole System EEP

Product #: 0208

1.0 fl oz (29.6 mL)

Ethanol 20%

PURPOSE

For the temporary relief of mild depression, energy loss, and anxiety. (**)